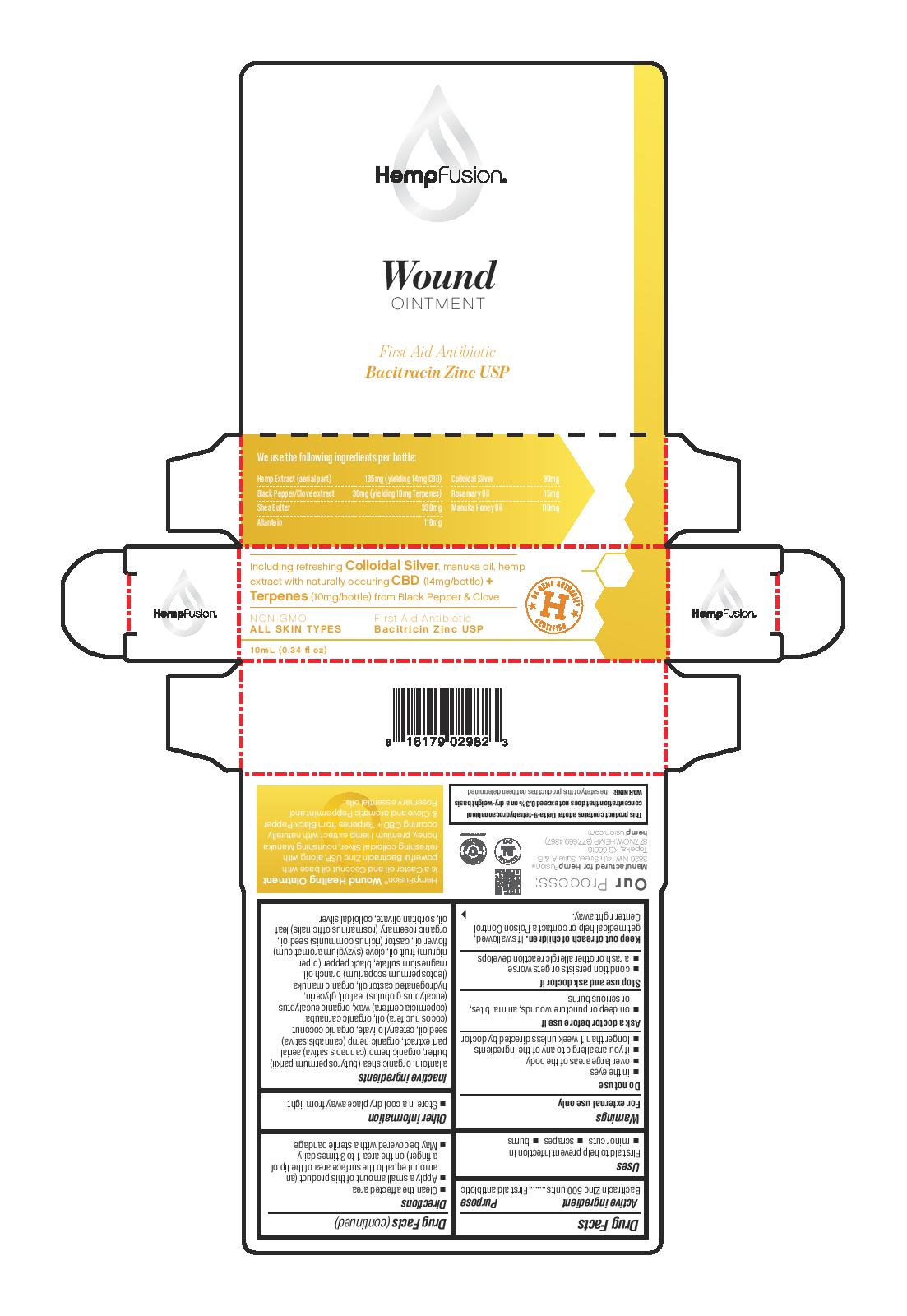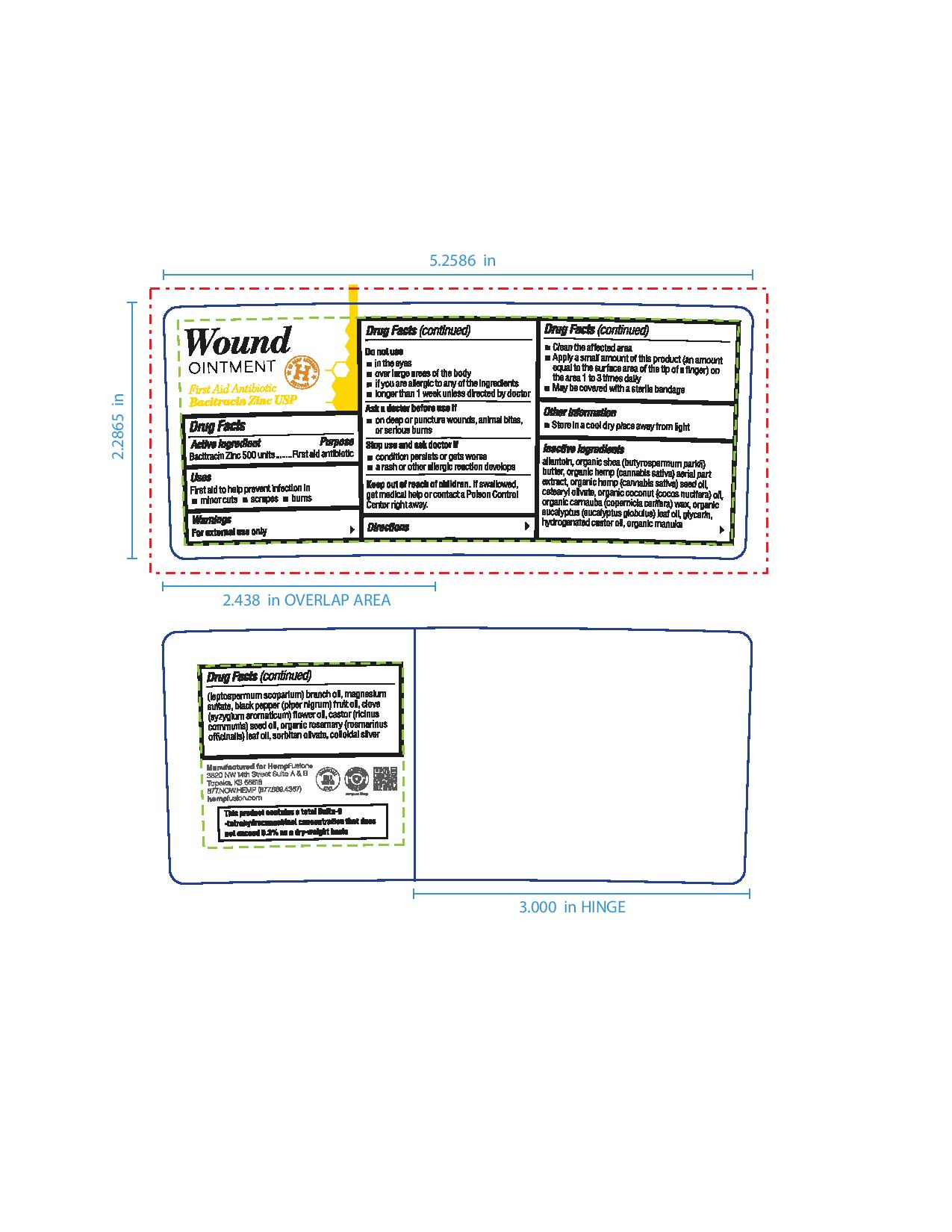 DRUG LABEL: Wound First Aid
NDC: 73672-982 | Form: OINTMENT
Manufacturer: HEMPFUSION, INC.
Category: otc | Type: HUMAN OTC DRUG LABEL
Date: 20210317

ACTIVE INGREDIENTS: BACITRACIN ZINC 500 [USP'U]/1 g
INACTIVE INGREDIENTS: HYDROGENATED CASTOR OIL; CETEARYL OLIVATE; CARNAUBA WAX; MANUKA OIL; BLACK PEPPER OIL; CLOVE OIL; CASTOR OIL; SILVER; CANNABIS SATIVA SEED OIL; EUCALYPTUS OIL; GLYCERIN; MAGNESIUM SULFATE, UNSPECIFIED FORM; ROSEMARY OIL; SORBITAN OLIVATE; ALLANTOIN; SHEA BUTTER; HEMP; COCONUT OIL

Wound Ointment

Active ingredient

Bacitracin Zinc 500 units

Purpose

Bacitracin Zinc 500 units........First aid antibiotic

Uses

First aid to help prevent infection in

- minor cuts
- scrapes
- burns

Warnings

For external use only

Do not use

- in the eyes
- over large areas of the body
- if you are allergic to any of the ingredients
- longer than 1 week unless directed by doctor

Ask a doctor before use if

- on deep or puncture wounds, animal bites, or serious burns

Stop use and ask doctor if

- condition persists or gets worse
- a rash or other allergic reaction develops

Keep out of reach of children. If swallowed, get medical help or contact a Poison Control Center right away.

Directions

- Clean the affected area
- Apply a small amount of this product (an amount equal to the surface area of the tip of a finger) on the area 1 to 3 times daily
- May be covered with a sterile bandage

Other information

- Store in a cool dry place away from light

Inactive ingredients

allantoin, organic shea (butyrospermum parkii) butter, organic hemp (cannabis sativa) aerial part extract, organic hemp (cannabis sativa) seed oil, cetearyl olivate, organic coconut (cocos nucifera) oil, organic carnauba (copernicia cerifera) wax, organic eucalyptus
(eucalyptus globulus) leaf oil, glycerin, hydrogenated castor oil, organic manuka (leptospermum scoparium) branch oil, magnesium sulfate, black pepper (piper nigrum) fruit oil, clove (syzygium aromaticum) flower oil, castor (ricinus communis) seed oil, organic rosemary (rosmarinus officinalis) leaf oil, sorbitan olivate, colloidal silver

Principal Display Panel

HempFusion

Wound

OINTMENT

First Aid Antibiotic

Bacitracin Zinc USP